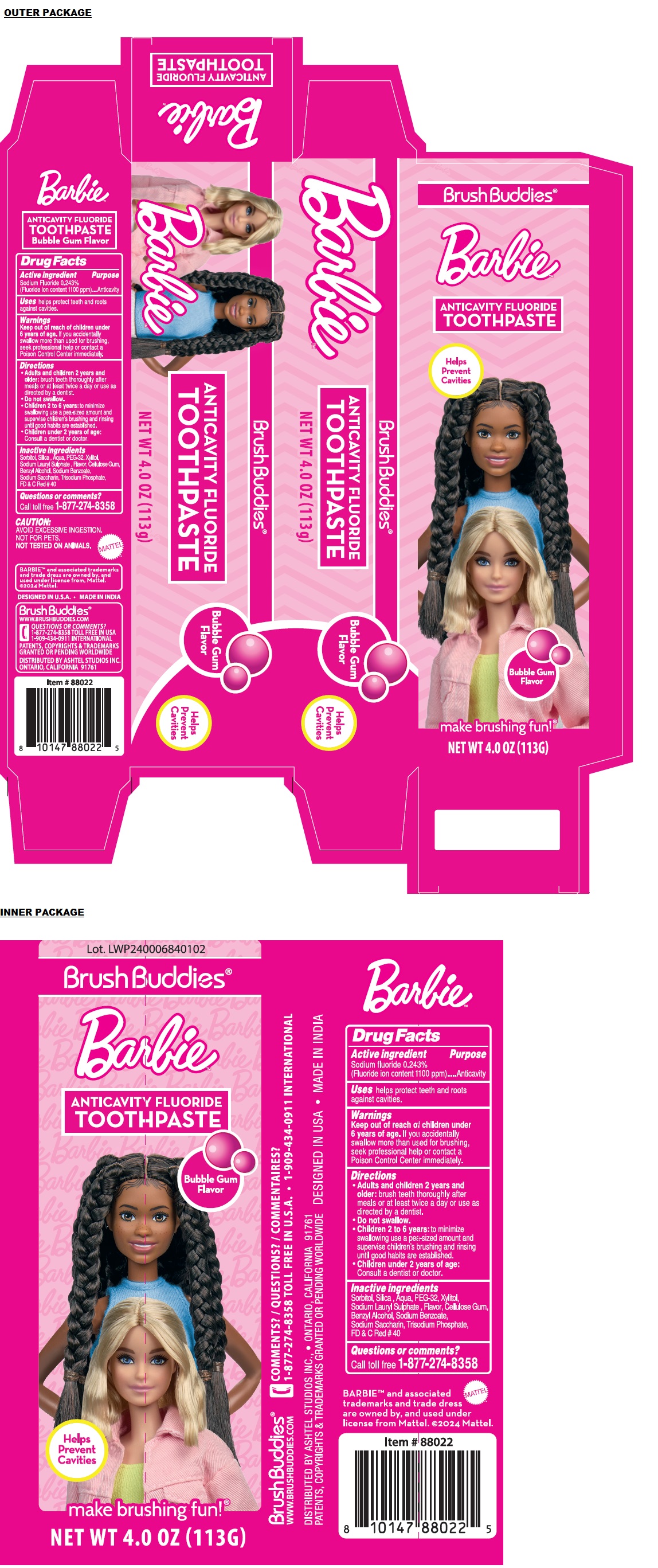 DRUG LABEL: Barbie Bubble Gum ANTICAVITY FLUORIDE
NDC: 70108-082 | Form: PASTE, DENTIFRICE
Manufacturer: Ashtel Studios Inc.
Category: otc | Type: HUMAN OTC DRUG LABEL
Date: 20240510

ACTIVE INGREDIENTS: SODIUM FLUORIDE 0.243 g/100 g
INACTIVE INGREDIENTS: SORBITOL; SILICON DIOXIDE; WATER; POLYETHYLENE GLYCOL 1600; XYLITOL; SODIUM LAURYL SULFATE; CARBOXYMETHYLCELLULOSE SODIUM, UNSPECIFIED; BENZYL ALCOHOL; SODIUM BENZOATE; SACCHARIN SODIUM; SODIUM PHOSPHATE, TRIBASIC, ANHYDROUS; FD&C RED NO. 40

Brush Buddies® BarbieTM ANTICAVITY FLUORIDE TOOTHPASTE

Active ingredient

Sodium Fluoride 0.243%
(Fluoride ion content 1100 ppm)

Purpose

Anticavity

Uses

helps protect teeth and roots against cavities.

Warnings

Keep out of reach of children under 6 years of age. If you accidentally swallow more than used for brushing, seek professional help or contact a Poison Control Center immediately.

Directions

• Adults and children 2 years and older: brush teeth thoroughly after meals or at least twice a day or use as directed by a dentist.
• Do not swallow.
• Children 2 to 6 years: to minimize swallowing use a pea-sized amount and supervise children's brushing and rinsing until good habits are established.
• Children under 2 years of age: Consult a dentist or doctor.

Inactive ingredients

Sorbitol, Silica, Aqua, PEG-32, Xylitol, Sodium Lauryl Sulfate, Flavor, Cellulose Gum, Benzyl Alcohol, Sodium Benzoate, Sodium Saccharin, Trisodium Phosphate, FD & C Red # 40

Questions or comments?

Call toll free 1-877-274-8358

BrushBuddies®
ANTICAVITY FLUORIDE TOOTHPASTE
Bubble Gum Flavor
Helps Prevent Cavities
make brushing fun!®

CAUTION:
AVOID EXCESSIVE INGESTION.
NOT FOR PETS.
NOT TESTED ON ANIMALS.

BARBIE™ and associated trademarks and trade dress are owned by, and used under license from, Mattel.
©2024 Mattel.
DESIGNED IN U.S.A. • MADE IN INDIA

Brush Buddies®
WWW.BRUSHBUDDIES.COM
1-909-434-0911 INTERNATIONAL
PATENTS, COPYRIGHTS & TRADEMARKS GRANTED OR PENDING WORLDWIDE
DISTRIBUTED BY ASHTEL STUDIOS INC.
ONTARIO, CALIFORNIA 91761